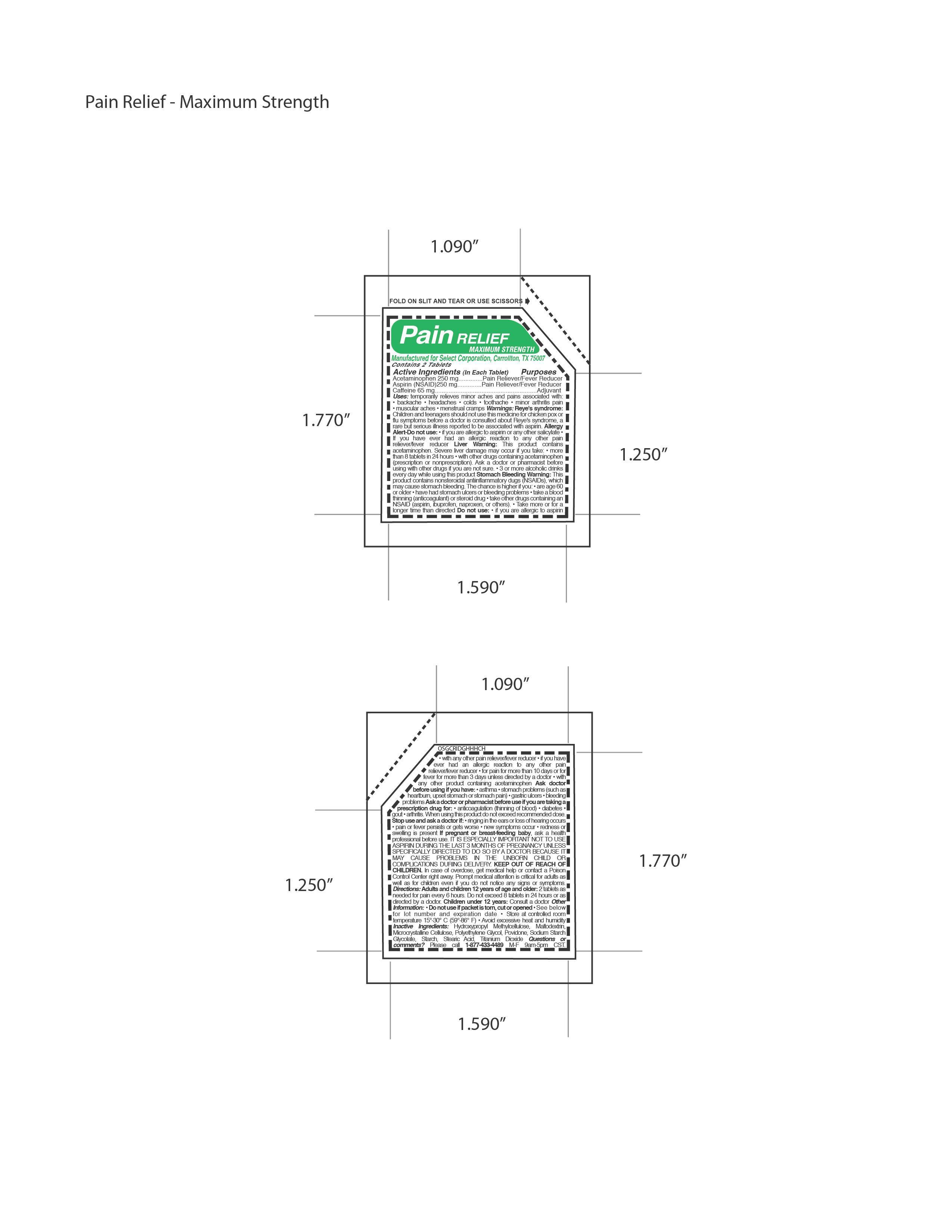 DRUG LABEL: Pain Relief Maximum Strength
                
NDC: 52904-468 | Form: TABLET, COATED
Manufacturer: Select Corporation
Category: otc | Type: HUMAN OTC DRUG LABEL
Date: 20121015

ACTIVE INGREDIENTS: ACETAMINOPHEN 250 mg/1 1; ASPIRIN 250 mg/1 1; CAFFEINE 65 mg/1 1
INACTIVE INGREDIENTS: POVIDONE K29/32; SODIUM STARCH GLYCOLATE TYPE A POTATO; CELLULOSE, MICROCRYSTALLINE; STEARIC ACID; MALTODEXTRIN; STARCH, CORN; POLYETHYLENE GLYCOL 300; TITANIUM DIOXIDE

Drug Facts

Active Ingredients

Acetaminophen 250 mg
Aspirin 250 mg
Caffeine 65 mg

PURPOSE

Pain Reliever, Fever Reducer

DOSAGE AND ADMINISTRATION

Directions: Adults and children 12 years of age and older: 2 tablets as
needed for pain every 6 hours. Do not exceed 8 tablets in 24 hours or as
directed by a doctor. Children under 12 years: Consult a doctor

INDICATIONS AND USAGE

Uses: temporarily relieves minor aches and pains associated with:
• backache • headaches • colds • toothache • minor arthritis pain
• muscular aches

Warnings: Reye's syndrome:
Children and teenagers should not use this medicine for chicken pox or
flu symptoms before a doctor is consulted about Reye's syndrome, a
rare but serious illness reported to be associated with aspirin. Allergy
Alert-Do not use: • if you are allergic to aspirin or any other salicylate •
If you have ever had an allergic reaction to any other pain
reliever/fever reducer Liver Warning: This product contains
acetaminophen. Severe liver damage may occur if you take: • more
than 8 tablets in 24 hours • with other drugs containing acetaminophen
(prescription or nonprescription). Ask a doctor or pharmacist before
using with other drugs if you are not sure. • 3 or more alcoholic drinks
every day while using this product Stomach Bleeding Warning: This
product contains nonsteroidal antiinflammatory dugs (NSAIDs), which
may cause stomach bleeding. The chance is higher if you: • are age 60
or older • have had stomach ulcers or bleeding problems • take a blood
thinning (anticoagulant) or steroid drug • take other drugs containing an
NSAID (aspirin, ibuprofen, naproxen, or others). • Take more or for a
longer time than directed Do not use: • if you are allergic to aspirin
• with any other pain reliever/fever reducer • if you have
ever had an allergic reaction to any other pain
reliever/fever reducer • for pain for more than 10 days or for
fever for more than 3 days unless directed by a doctor • with
any other product containing acetaminophen Ask doctor
before using if you have: • asthma • stomach problems (such as
heartburn, upset stomach or stomach pain) • gastric ulcers • bleeding
problems Ask a doctor or pharmacist before use if you are taking a
prescription drug for: • anticoagulation (thinning of blood) • diabetes •
gout • arthritis. When using this product do not exceed recommended dose.
Stop use and ask a doctor if: • ringing in the ears or loss of hearing occurs
• pain or fever persists or gets worse • new symptoms occur • redness or
swelling is present

PREGNANCY OR BREAST FEEDING

If pregnant or breast-feeding baby, ask a health
professional before use. IT IS ESPECIALLY IMPORTANT NOT TO USE
ASPIRIN DURING THE LAST 3 MONTHS OF PREGNANCY UNLESS
SPECIFICALLY DIRECTED TO DO SO BY A DOCTOR BECAUSE IT
MAY CAUSE PROBLEMS IN THE UNBORN CHILD OR
COMPLICATIONS DURING DELIVERY.

KEEP OUT OF REACH OF CHILDREN.

INACTIVE INGREDIENT

IInactive Ingredients: Hydroxypropyl Methylcellulose, Maltodextrin,
Microcrystalline Cellulose, Polyethylene Glycol, Povidone, Sodium Starch
Glycolate, Starch, Stearic Acid, Titanium Dioxide

PACKAGE LABEL

MM1